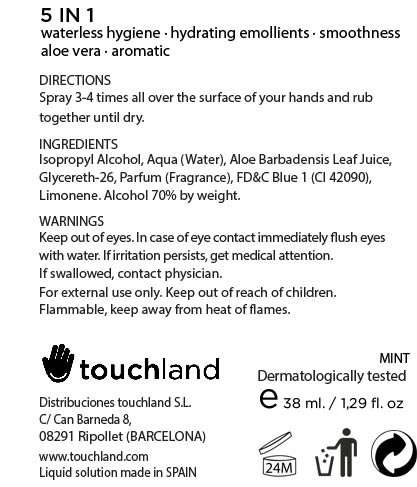 DRUG LABEL: TOUCHLAND kub2go Hand Sanitizer Mint
NDC: 70083-001 | Form: LIQUID
Manufacturer: Distribuciones Touchland S.L.
Category: otc | Type: HUMAN OTC DRUG LABEL
Date: 20150917

ACTIVE INGREDIENTS: ISOPROPYL ALCOHOL 0.7 mL/1 mL
INACTIVE INGREDIENTS: LIMONENE, (+)-; WATER; GLYCERETH-26; FD&C BLUE NO. 1; ALOE VERA LEAF

Inactive ingredients

Aqua (Water), Aloe Barbadensis Leaf Juice, Glycereth-26,
Parfum (Fragrance), FD&C Blue 1 (CI 42090), Limonene

Purpose

Antiseptic

Active ingredients

Isopropyl alcohol 70% (W/W)

Uses

Kills 99.99% of all disease causing germs on contact, and protects and restores moisture.

Warnings

Keep out of eyes. In case of eye contact immediately flush eyes with water. If irritation persists, get medical attention. If swallowed, contact physician.

For external use only. Keep out of reach of children.

Flammable, keep away from heat of flames.

Directions

Spray 3-4 times all over the surface of your hands and rub together until dry. Supervise children in the use of this product.